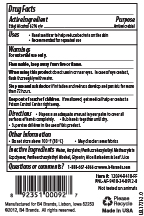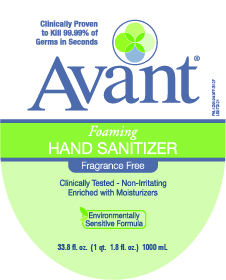 DRUG LABEL: Avant Foaming Hand Sanitizer
NDC: 68306-109 | Form: LIQUID
Manufacturer: B4 Ventures LLC
Category: otc | Type: HUMAN OTC DRUG LABEL
Date: 20241001

ACTIVE INGREDIENTS: ALCOHOL 62 mL/100 mL
INACTIVE INGREDIENTS: 2-(PERFLUOROHEXYL)ETHANOL; WATER; ALOE VERA LEAF; BUTYL ACRYLATE/METHYL METHACRYLATE/PERFLUOROHEXYLETHYL METHACRYLATE COPOLYMER (SALUS AF); GLYCERIN

B4 Brands: Avant Foaming Hand Sanitizer - Fragrance Free

Active Ingredient

Ethanol 62% v/v

Purpose

Antimicrobial

Uses

- Hand sanitizer to help reduce bacteria on the skin
- Recommended for repeated use

Warnings

For external use only.

Flammable, keep away from fire or flame.

When using this product do not use in or near eyes. In case of eye contact, flush thoroughly with water.

Stop use and ask doctor if irritation and redness develop and persists for more than 72 hours.

Keep out of reach of children. If swallowed, get medical help or contact a Poison Control Center right away.

Directions

Dispense an adequate amount in your palm to cover all surfaces of hands completely.

Rub hands together until dry.

Supervise children in the use of this product.

Other Information

- Do not store above 100 ºF (38 ºC)
- May discolor some fabrics

Inactive Ingredients

Water, Acrylates/Perfluorohexylethyl Methacrylate Copolymer, Perfluorohexylethyl Alcohol, Glycerin, Aloe Barbadensis Leaf Juice

Questions or comments?

1-888-667-6066 or www. b4brands.com